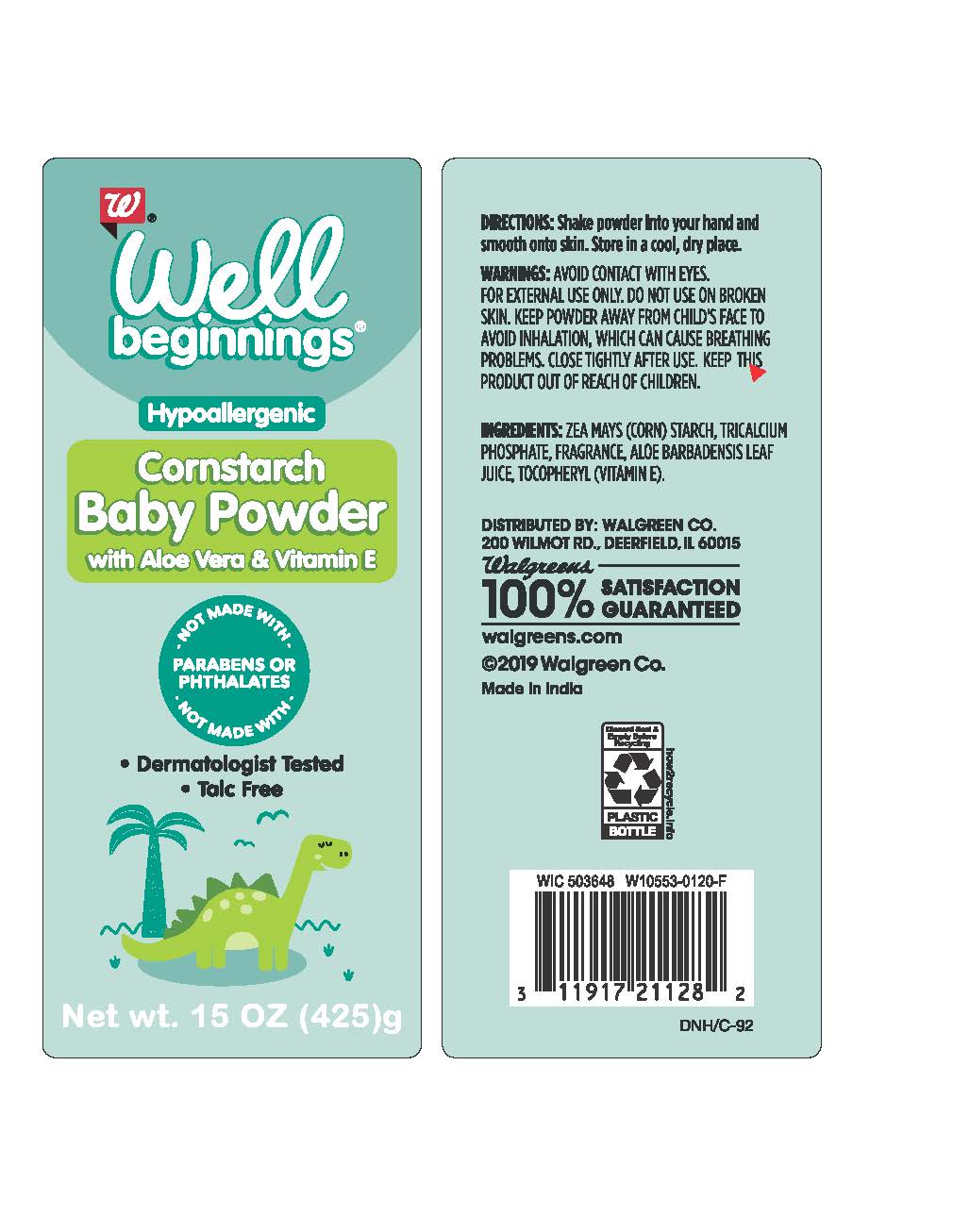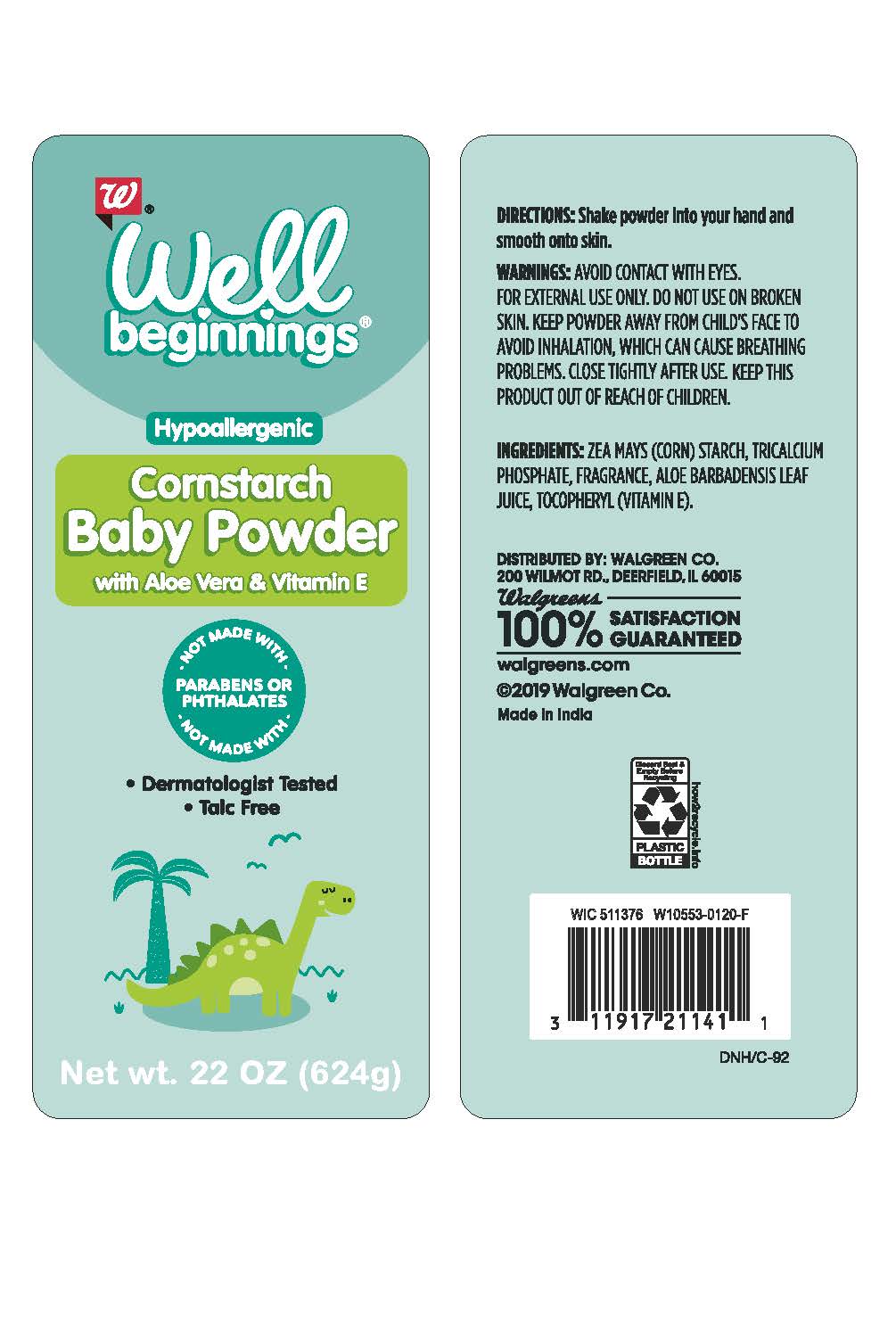 DRUG LABEL: Pure Cornstarch Baby
NDC: 0363-0911 | Form: POWDER
Manufacturer: Walgreen Company
Category: otc | Type: HUMAN OTC DRUG LABEL
Date: 20240325

ACTIVE INGREDIENTS: STARCH, CORN 99 g/100 g
INACTIVE INGREDIENTS: TRICALCIUM PHOSPHATE; ALOE VERA LEAF; .ALPHA.-TOCOPHEROL

Walgreens® PURE CORNSTARCH BABY POWDER

Active ingredient

Corn Starch (Zea Mays) 99%

Purpose

Skin Protectant

Uses

- gently absorbs excess moisture for soft, dry skin.
- helps protect against irritating friction, leaving your skin feeling cool and comfortable.

Warnings

Avoid contact with eyes.

For external use only.

Do not use on broken skin.

Keep powder away from child’s face to avoid inhalation, which can cause breathing problems.

Close tightly after use.

Keep this product out of reach of children.

Directions

Shake powder into your hand and smooth onto skin.

Storage

Store in a cool, dry place.

Inactive ingredients

Tricalcium Phosphate, Fragrance, Aloe Barbadensis Leaf Juice, Tocopheryl (Vitamin E).

Package/Label Principal Display Panel

Pure Cornstarch Baby Powder

Gently absorbs excess moisture for soft, dry skin

Clinically Tested

NET WT 15 OZ (425 g)